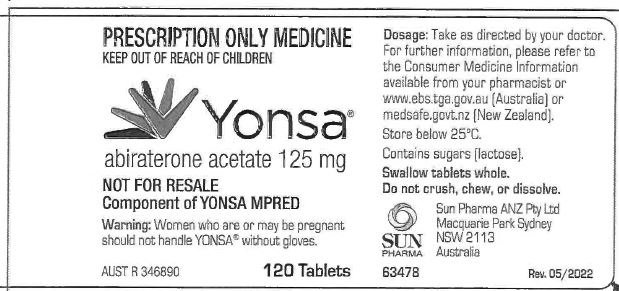 DRUG LABEL: YONSA
NDC: 11014-0566 | Form: TABLET
Manufacturer: Catalent Pharma Solutions, LLC
Category: prescription | Type: HUMAN PRESCRIPTION DRUG LABEL
Date: 20250922

ACTIVE INGREDIENTS: ABIRATERONE ACETATE 125 mg/1 1

YONSA (abiraterone acetate) tablets